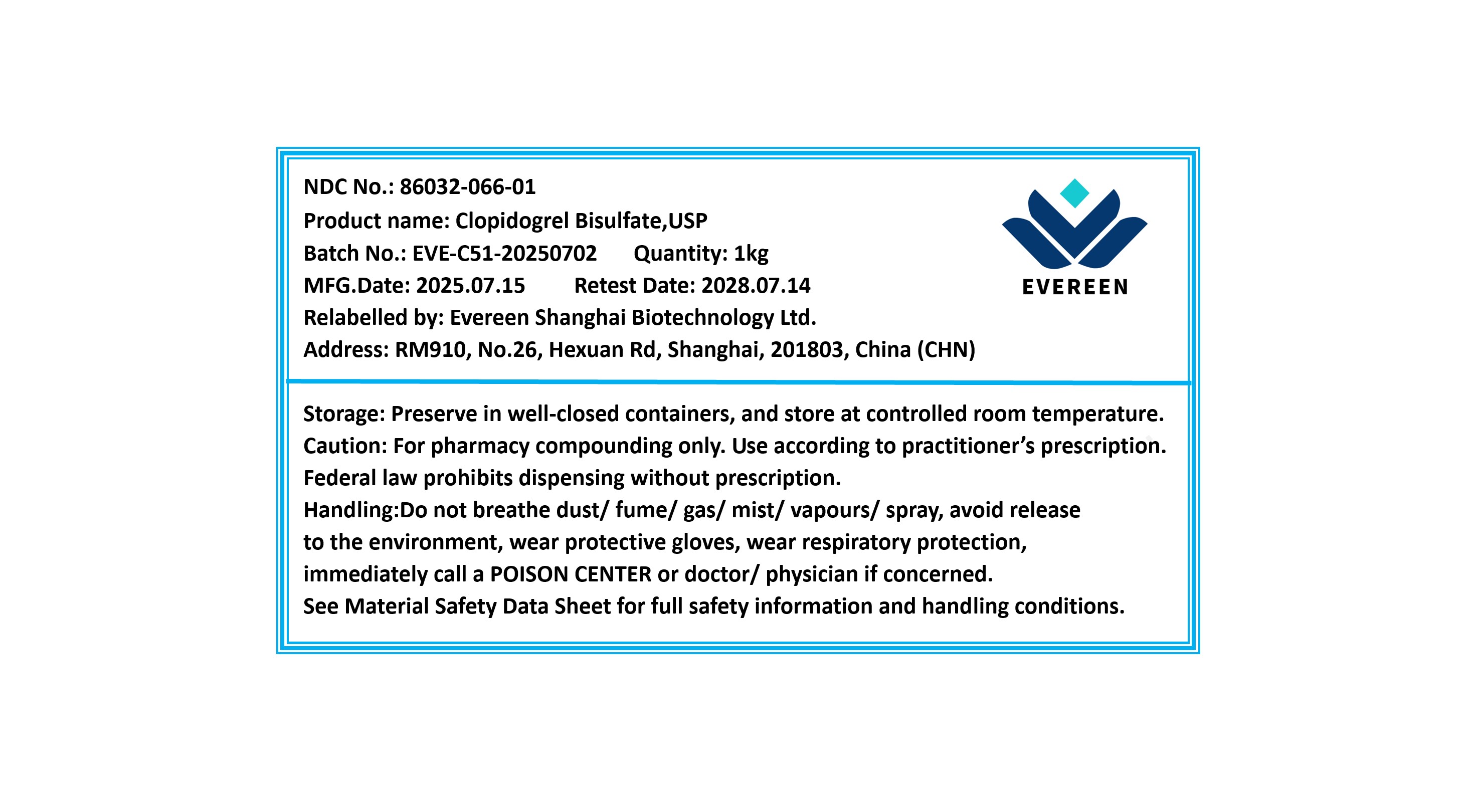 DRUG LABEL: Clopidogrel Bisulfate
NDC: 86032-066 | Form: POWDER
Manufacturer: Evereen Shanghai Biotechnology Ltd.
Category: other | Type: BULK INGREDIENT - ANIMAL DRUG
Date: 20260104

ACTIVE INGREDIENTS: CLOPIDOGREL BISULFATE 1000 g/1 g

Clopidogrel Bisulfate